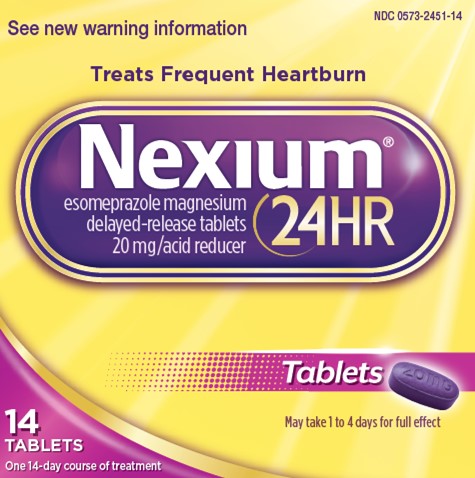 DRUG LABEL: Nexium 24HR
NDC: 0573-2451 | Form: TABLET
Manufacturer: Haleon US Holdings LLC
Category: otc | Type: HUMAN OTC DRUG LABEL
Date: 20240319

ACTIVE INGREDIENTS: ESOMEPRAZOLE MAGNESIUM 20 mg/1 1
INACTIVE INGREDIENTS: STARCH, CORN; CROSPOVIDONE (120 .MU.M); D&C RED NO. 27; FD&C BLUE NO. 2; FD&C RED NO. 40; GLYCERYL MONOSTEARATE; HYDROXYPROPYL CELLULOSE (1600000 WAMW); HYPROMELLOSE, UNSPECIFIED; MAGNESIUM STEARATE; METHACRYLIC ACID - METHYL METHACRYLATE COPOLYMER (1:1); MICA; MICROCRYSTALLINE CELLULOSE; PARAFFIN; POLYETHYLENE GLYCOL, UNSPECIFIED; POLYSORBATE 80; SODIUM STEARYL FUMARATE; SUCROSE; TALC; TITANIUM DIOXIDE; TRIETHYL CITRATE

Drug Facts

Active ingredient (in each tablet)

Esomeprazole 20 mg

(Each delayed-release tablet corresponds to 22.3 mg esomeprazole magnesium trihydrate)

Purpose

Acid reducer

Uses

- treats frequent heartburn (occurs 2 or moredays a week)
- not intended for immediate relief of heartburn; this drug may take 1 to 4 days for full effect

Warnings

Allergy alert

- Do not use if you are allergic to esomeprazole
- Esomeprazole may cause severe skin reactions. Symptoms include:
- skin reddening
- blisters
- rash

If an allergic reaction occurs, stop use and seek medical attention right away.

Do not use if you have:

- trouble or pain swallowing food, vomiting with blood, or bloody or black stools
- heartburn with lightheadedness, sweating or dizziness
- chest pain or shoulder pain with shortness of breath; sweating; pain spreading to arms, neck or shoulders; or lightheadedness
- frequent chest pain

These may be signs of a serious condition. See your doctor.

Ask a doctor before use if you have

- had heartburn over 3 months. This may be a sign of a more serious condition.
- frequent wheezing, particularly with heartburn
- unexplained weight loss
- nausea or vomiting
- stomach pain

Ask a doctor or pharmacist before use if you are

- taking a prescription drug. Acid reducers may interact with certain prescription drugs.

Stop use and ask a doctor if

- your heartburn continues or worsens
- you need to take this product for more than 14 days
- you need to take more than 1 course of treatment every 4 months
- you get diarrhea
- you develop a rash or joint pain

PREGNANCY OR BREAST FEEDING

If pregnant or breast-feeding,ask a health professional before use.

Keep out of reach of children.In case of overdose, get medical help or contact a Poison Control Center right away.

Directions

- adults 18 years of age and older
- this product is to be used once a day (every 24 hours), every day for 14 days
- may take 1 to 4 days for full effect
  14-Day Course of Treatment
  - swallow 1 tablet with a glass of water before eating in the morning
  - take every day for 14 days
  - do not take more than 1 tablet a day
  - swallow whole. Do not crush or chew tablets.
  - do not use for more than 14 days unless directed by your doctor
- Repeated 14-Day Courses (if needed)
  1. you may repeat a 14-day course every 4 months
  2. do not take for more than 14 days or more often than every 4 months unless directed by a doctor
- children under 18 years of age: ask a doctor before use. Heartburn in children may sometimes be caused by a serious condition.

Other Information

- read the directions and warnings before use
- keep the carton. It contains important information.
- store at 20-25°C (68-77°F)

Inactive ingredients

corn starch, crospovidone, D&C red no. 27 aluminum lake, FD&C blue no. 2 aluminum lake, FD&C red no. 40 aluminum lake, glyceryl monostearate, hydroxypropyl cellulose, hypromellose, magnesium stearate, methacrylic acid copolymer, mica, microcrystalline cellulose, paraffin, polyethylene glycol, polysorbate 80, sodium stearyl fumarate, sucrose, talc, titanium dioxide, triethyl citrate

Questions or comments?

call toll-free weekdays 9 AM to 5 PM EST at 1-866-226-1600

Additional Information

KEEP CARTON FOR COMPLETE WARNINGS AND IMPORTANT INFORMATION.

Do Not Use if seal under bottle cap imprinted with “SEALED for YOUR PROTECTION”

or yellow band around the center of each capsule is broken or missing.

Tips for Managing Heartburn

- Avoid foods or drinks that are more likely to cause heartburn, such as rich, spicy, fatty
- and fried foods, chocolate, caffeine, alcohol and even some acidic fruits and vegetables.
- Eat slowly and do not eat big meals.
- Do not eat late at night or just before bedtime.
- Do not lie flat or bend over soon after eating.
- Raise the head of your bed.
- Wear loose-fitting clothing around your stomach.
- If you are overweight, lose weight.
- If you smoke, quit smoking

Distributed by: GSK Consumer Healthcare,

Warren, NJ 07059

©2022 GSK group of companies or its licensor

Made in France

For most recent product information, visit www.Nexium24HR.com

Nexium is a registered trademark of AstraZeneca AB and is used under license.

PRINCIPAL DISPLAY PANEL

NDC 0573-2451-14

See new warning information

Treats Frequent Heartburn

Nexium®
24HR

esomeprazole magnesium

delayed-release tablets
20 mg/acid reducer

Tablets

May take 1 to 4 days for full effect

14
TABLETS

One 14-day course of treatment

000078388 Front Carton